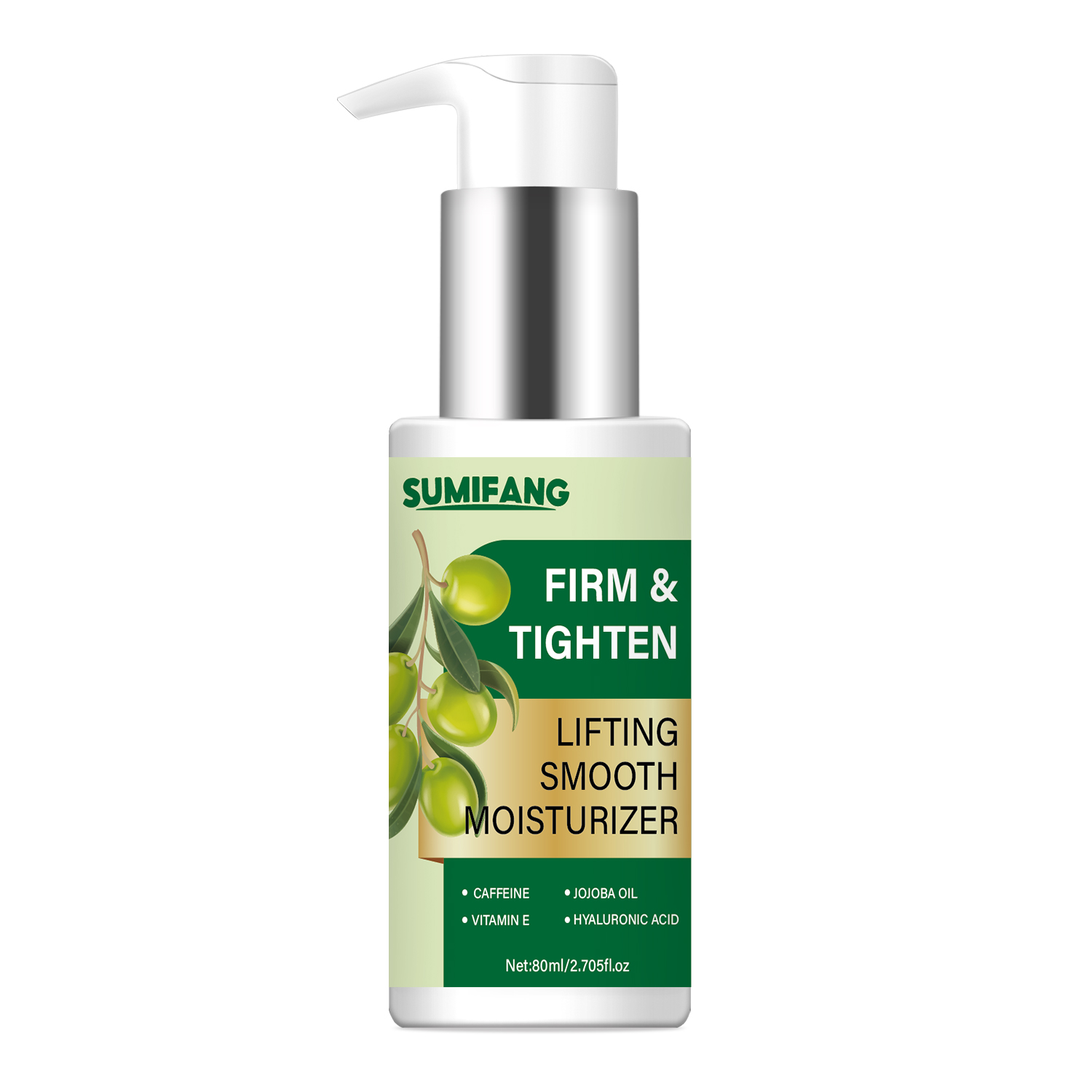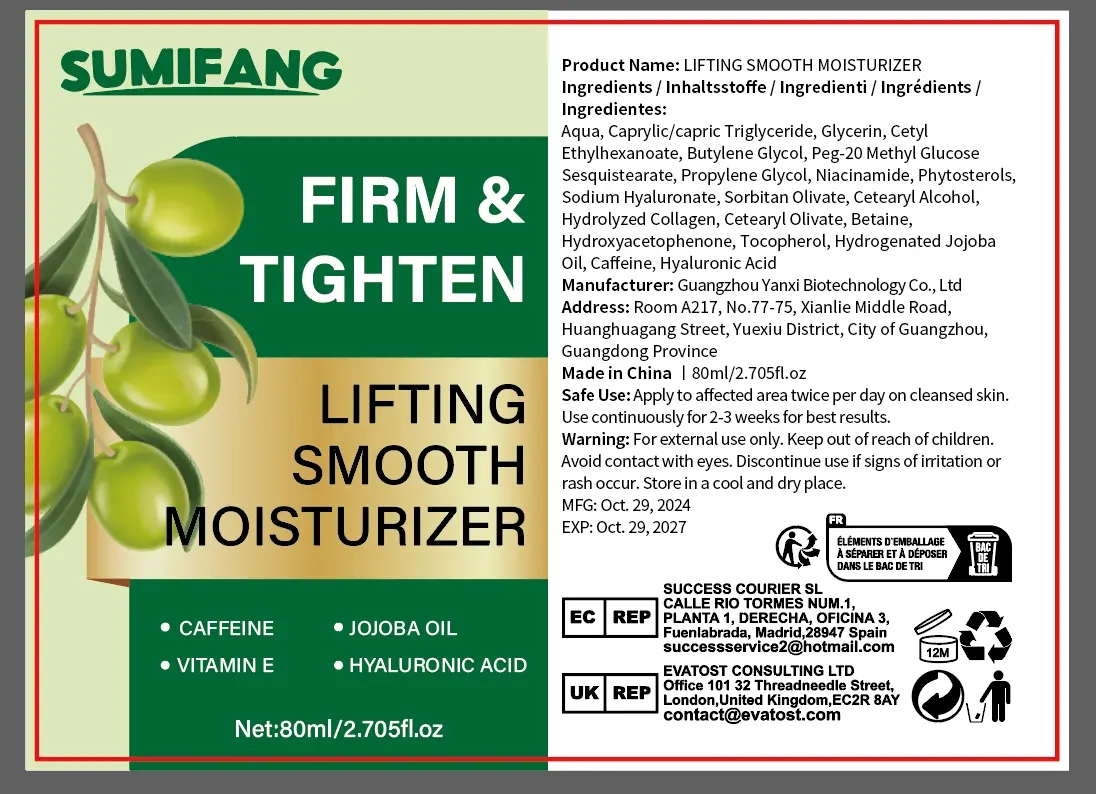 DRUG LABEL: LIFTING SMOOTH MOISTURIZER
NDC: 84025-256 | Form: CREAM
Manufacturer: Guangzhou Yanxi Biotechnology Co., Ltd
Category: otc | Type: HUMAN OTC DRUG LABEL
Date: 20241109

ACTIVE INGREDIENTS: GLYCERIN 3 mg/100 mL; CAPRYLIC/CAPRIC TRIGLYCERIDE 5 mg/100 mL
INACTIVE INGREDIENTS: WATER

DOSAGE AND ADMINISTRATION

Apply to affected area twice per day on cleansed skin.
Use continuously for 2-3 weeks for best results.

WARNINGS

keep out of children

INACTIVE INGREDIENT

Aqua

INDICATIONS AND USAGE

for face care

keep out of children

PURPOSE

FIRM &TIGHTEN FACE